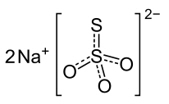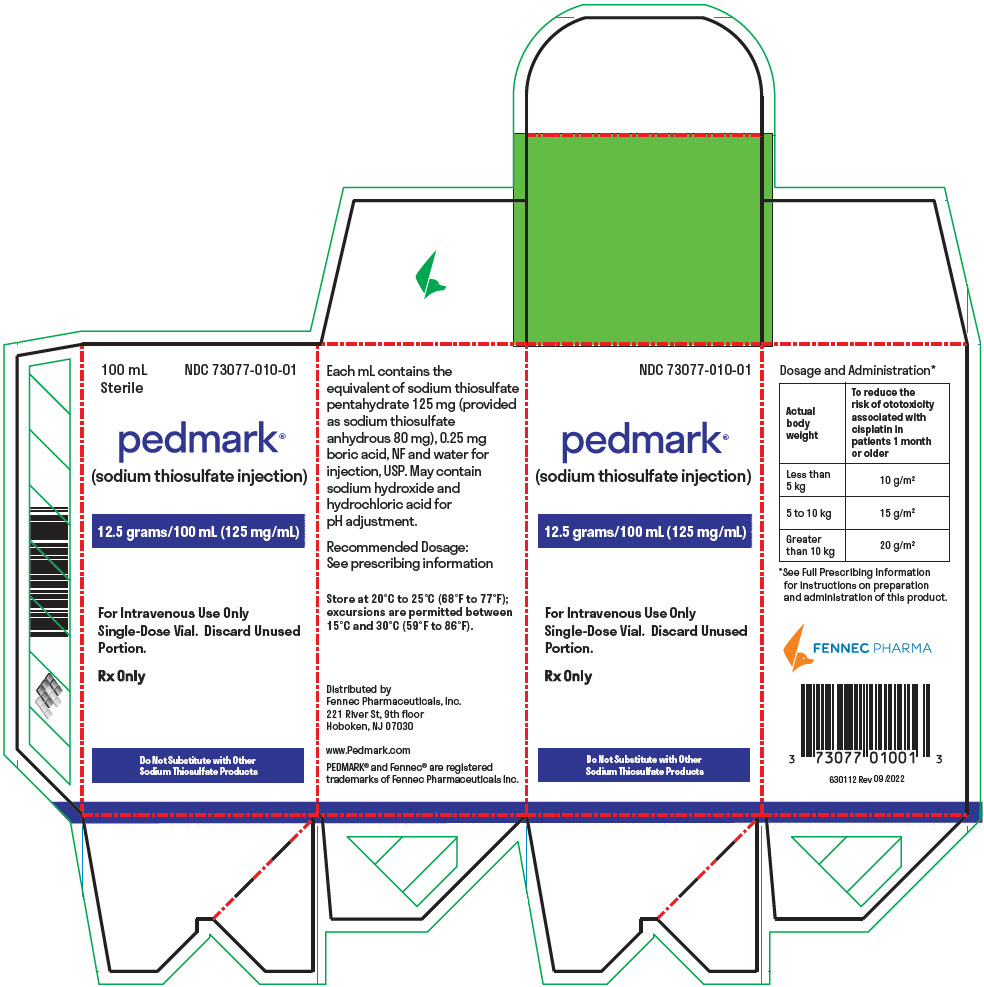 DRUG LABEL: PEDMARK
NDC: 73077-010 | Form: INJECTION, SOLUTION
Manufacturer: Fennec Pharmaceuticals Inc.
Category: prescription | Type: HUMAN PRESCRIPTION DRUG LABEL
Date: 20251027

ACTIVE INGREDIENTS: SODIUM THIOSULFATE 12.5 g/100 mL
INACTIVE INGREDIENTS: BORIC ACID; SODIUM HYDROXIDE; HYDROCHLORIC ACID

HIGHLIGHTS OF PRESCRIBING INFORMATION

These highlights do not include all the information needed to use PEDMARK safely and effectively. See full prescribing information for PEDMARK.
PEDMARK® (sodium thiosulfate injection), for intravenous use
Initial U.S. Approval: 1992

1 INDICATIONS AND USAGE

PEDMARK is indicated to reduce the risk of ototoxicity associated with cisplatin in pediatric patients 1 month of age and older with localized, non-metastatic solid tumors. (1)

Limitations of Use:

The safety and efficacy of PEDMARK have not been established when administered following cisplatin infusions longer than 6 hours. PEDMARK may not reduce the risk of ototoxicity when administered following longer cisplatin infusions, because irreversible ototoxicity may have already occurred.

2 DOSAGE AND ADMINISTRATION

PEDMARK is not substitutable with other sodium thiosulfate products. (2)

The recommended dose of PEDMARK is based on surface area according to actual body weight.

- Administer PEDMARK as an intravenous infusion over 15 minutes starting 6 hours after completion of cisplatin infusion.
- For multiday cisplatin regimens, administer PEDMARK 6 hours after each cisplatin infusion but at least 10 hours before the next cisplatin infusion.
- Do not start PEDMARK if less than 10 hours before starting the next cisplatin infusion (2)

Actual Body Weight | PEDMARK Dose
Less than 5 kg | 10 g/m^2
5 to 10 kg | 15 g/m^2
Greater than 10 kg | 20 g/m^2

3 DOSAGE FORMS AND STRENGTHS

Injection: 12.5 grams/100 mL in a single-dose vial. (3)

4 CONTRAINDICATIONS

History of severe hypersensitivity to sodium thiosulfate or any components. (4)

5 WARNINGS AND PRECAUTIONS

- Hypersensitivity: Immediately discontinue PEDMARK and institute appropriate care. Administer premedications before each subsequent dose. PEDMARK may contain sodium sulfite; patients with sulfite sensitivity may have hypersensitivity reactions. (5.1)
- Hypernatremia and Hypokalemia: PEDMARK is not indicated for use in pediatric patients less than 1 month of age. Monitor serum sodium and potassium at baseline and as clinically indicated. Withhold PEDMARK in patients with serum sodium greater than 145 mmol/L (5.2)
- Nausea and Vomiting: Administer antiemetics prior to each PEDMARK administration. (5.3)

6 ADVERSE REACTIONS

- Most common adverse reactions (≥ 25% with difference between arms of >5% compared to cisplatin alone) in SIOPEL 6 are vomiting, nausea, decreased hemoglobin, and hypernatremia. (6)
- Most common adverse reaction (≥25% with difference between arms of >5% compared to cisplatin alone) in COG ACCL0431 is hypokalemia. (6)

To report SUSPECTED ADVERSE REACTIONS, contact Fennec Pharmaceuticals, Inc. at 1-833-336-6321, or FDA at 1-800-FDA-1088 or www.fda.gov/medwatch.

8 USE IN SPECIFIC POPULATIONS

Renal Impairment: Monitor for signs and symptoms of hypernatremia and hypokalemia more closely if the glomerular filtration rate (GFR) falls below 60 mL/min/1.73m^2. (5.2, 8.6)

FULL PRESCRIBING INFORMATION

1 INDICATIONS AND USAGE

PEDMARK is indicated to reduce the risk of ototoxicity associated with cisplatin in pediatric patients 1 month of age and older with localized, non-metastatic solid tumors.

Limitations of Use

The safety and efficacy of PEDMARK have not been established when administered following cisplatin infusions longer than 6 hours. PEDMARK may not reduce the risk of ototoxicity when administered following longer cisplatin infusions, because irreversible ototoxicity may have already occurred.

2 DOSAGE AND ADMINISTRATION

2.1 Important Dosing Information

PEDMARK is not substitutable with other sodium thiosulfate products.

Ensure serum sodium level is within normal range prior to initiating PEDMARK [see Warnings and Precautions (5.2)].

2.2 Recommended Dosage and Administration

The recommended dose of PEDMARK is based on surface area according to actual body weight as summarized in Table 1.

Table 1. Recommended Dose for PEDMARK
Actual Body Weight | PEDMARK Dose
Less than 5 kg | 10 g/m^2
5 to 10 kg | 15 g/m^2
Greater than 10 kg | 20 g/m^2

Administer PEDMARK as an intravenous infusion over 15 minutes, following cisplatin infusions that are 1 to 6 hours in duration [see Indications and Usage (1)].

Infuse PEDMARK as described below to minimize the potential interference with the antitumor activity of cisplatin [see Clinical Pharmacology (12.1), Clinical Studies (14)].

- Administer PEDMARK 6 hours after completion of a cisplatin infusion.
- For multiday cisplatin regimens, administer PEDMARK 6 hours after completion of each cisplatin infusion and at least 10 hours before the next cisplatin infusion. Do not administer PEDMARK if the next cisplatin infusion is scheduled to begin in less than 10 hours [see Clinical Pharmacology (12.3), Clinical Studies (14)].

2.3 Recommended Premedications

Administer antiemetics before each PEDMARK infusion [see Warnings and Precautions (5.3)].

For patients who experience a hypersensitivity reaction, administer antihistamines and glucocorticoids (if appropriate) before each subsequent PEDMARK infusion [see Warnings and Precautions (5.1)].

2.4 Dosage Modifications for Adverse Reactions

The recommended dosage modifications for adverse reactions are provided in Table 2.

Table 2. Recommended PEDMARK Dosage Modifications for Adverse Reactions
Adverse Reaction | Severity | Dosage Modification
Hypersensitivity [see Warnings and Precautions (5.1)] | Grade 3 or 4 | Permanently discontinue PEDMARK.
Hypernatremia [see Warnings and Precautions (5.2)] | >145 mmol/L | Withhold PEDMARK until sodium is within normal limits. Resume at the same dose.
Hypokalemia [see Warnings and Precautions (5.2)] | Grade 3 or 4 | Withhold PEDMARK until potassium is within normal limits. Resume at the same dose.
Other Adverse Reactions [see Adverse Reactions (6.1)] | Grade 3 | Withhold until ≤ Grade 1. Resume at the same dose.
Other Adverse Reactions [see Adverse Reactions (6.1)] | Grade 4 | Permanently discontinue PEDMARK.

2.5 Preparation

- Calculate the dose (grams) and determine the number of vial(s) needed.
- Visually inspect the contents of the vial for particulate matter and discoloration. Discard the vial(s) if discolored or contains visible particulates.
- Withdraw the calculated dose from the vial(s) into a syringe or transfer the calculated dose into an empty infusion bag.
- Use immediately after withdrawing into a syringe or transferring to an empty infusion bag. If not used immediately, PEDMARK can be stored in an infusion bag for no more than 18 hours at 20°C to 22°C (68°F to 72°F). Discard unused portion.

No incompatibilities have been observed between PEDMARK with infusion bags made of polyvinyl chloride, ethylene vinyl acetate, or polyolephin.

3 DOSAGE FORMS AND STRENGTHS

Injection: 12.5 grams/100 mL (125 mg/mL) clear, colorless solution in a single-dose vial

4 CONTRAINDICATIONS

PEDMARK is contraindicated in patients with history of a severe hypersensitivity to sodium thiosulfate or any of its components [see Warnings and Precautions (5.1)].

5 WARNINGS AND PRECAUTIONS

5.1 Hypersensitivity

Hypersensitivity reactions occurred in 8% to 13% of patients in clinical trials [see Adverse Reactions (6.1)].

PEDMARK is contraindicated in patients with a history of severe hypersensitivity to sodium thiosulfate or its components [see Contraindications (4)].

Monitor patients for hypersensitivity reactions. Immediately discontinue PEDMARK and institute appropriate care if a hypersensitivity reaction occurs [see Dosage and Administration (2.4)]. Administer antihistamines or glucocorticoids (if appropriate) before each subsequent administration of PEDMARK [see Dosage and Administration (2.3)].

PEDMARK may contain sodium sulfite. Sulfite exposure can cause hypersensitivity reactions, including anaphylactic symptoms and life-threatening or severe asthma episodes, in patients with sulfite sensitivity. The overall prevalence of sulfite sensitivity in the general population is unknown; sulfite sensitivity is seen more frequently in people with asthma compared to people without asthma.

5.2 Hypernatremia and Hypokalemia

At the recommended dosage of PEDMARK, a 20 g/m^2 dose delivers a sodium load of 162 mmol/m^2, a 15 g/m^2 dose delivers a sodium load of 121 mmol/m^2 and a 10 g/m^2 dose delivers a sodium load of 81 mmol/m^2.

Hypernatremia occurred in 12% to 26% of patients in clinical trials, including a single Grade 3 case. Hypokalemia occurred in 15% to 27% of patients in clinical trials, with Grade 3 or 4 occurring in 9% to 27% [see Adverse Reactions (6.1)].

Pediatric patients younger than 1 month have less well-developed sodium homeostasis compared to other pediatric patients. PEDMARK is not indicated and not recommended for use in pediatric patients younger than 1 month of age.

Monitor serum sodium and potassium levels at baseline and as clinically indicated. Do not initiate PEDMARK infusions in patients with baseline serum sodium greater than 145 mmol/L [see Clinical Pharmacology (12.2), Dosage and Administration (2.3)].

Withhold PEDMARK in patients with serum sodium greater than 145 mmol/L [see Clinical Pharmacology (12.2), Dosage and Administration (2.4)].

Monitor for signs and symptoms of hypernatremia and hypokalemia. Provide supportive care and supplementation as appropriate.

5.3 Nausea and Vomiting

Nausea occurred in 8% to 40% of patients in clinical trials, with Grade 3 or 4 in 3.8 to 8%. Vomiting occurred in 7% to 85% of patients in clinical trials, with Grade 3 or 4 in 7% to 8% [see Adverse Reactions (6.1)].

Administer antiemetics prior to each PEDMARK administration [see Dosage and Administration (2.3)]. Provide additional antiemetics and supportive care as appropriate.

6 ADVERSE REACTIONS

The following clinically significant adverse reactions are described elsewhere in the labeling:

- Hypersensitivity [see Warnings and Precautions (5.1)]
- Hypernatremia and Hypokalemia [see Warnings and Precautions (5.2)]
- Nausea and Vomiting [see Warnings and Precautions (5.3)]

6.1 Clinical Trials Experience

Because clinical trials are conducted under widely varying conditions, adverse reaction rates observed in the clinical trials of a drug cannot be directly compared to rates in the clinical trials of another drug and may not reflect the rates observed in practice.

SIOPEL 6

The safety of PEDMARK was evaluated in SIOPEL 6 [see Clinical Studies (14)]. Patients received cisplatin-based chemotherapy with or without PEDMARK administered at a dose of 10 g/m^2, 15 g/m^2, or 20 g/m^2 (depending on body weight) as an intravenous infusion over 15 minutes starting 6 hours after completion of each cisplatin infusion. Patients received PEDMARK for a median of 6 cycles (range: 2 to 8 cycles) during a median of 94 days (range: 2.1 to 5.2 months) of cisplatin-based chemotherapy.

Serious adverse reactions occurred in 40% of patients who received PEDMARK in combination with cisplatin-based chemotherapy. Serious adverse reactions in >5% of patients who received PEDMARK included infection, decreased neutrophil count, and pyrexia.

PEDMARK was permanently discontinued due to an adverse reaction in 1 patient; this patient discontinued PEDMARK for Grade 2 hypersensitivity.

The most common adverse reactions (≥25% with difference between arms of >5% compared to cisplatin alone) were vomiting, nausea, decreased hemoglobin, and hypernatremia.

Table 3 summarizes the adverse reactions reported in SIOPEL 6.

Table 3. Adverse Reactions (≥10%) in Patients Who Received PEDMARK and Cisplatin with a Difference Between Arms of >5% Compared to Cisplatin Alone in SIOPEL 6
Adverse Reaction | PEDMARK + Cisplatin (N = 53) |  | Cisplatin Alone (N = 56)
Adverse Reaction | All Grades (%) | Grade 3 or 4 (%) | All Grades (%) | Grade 3 or 4 (%)
Gastrointestinal disorders
Vomiting | 85 | 8 | 54 | 3.6
Nausea | 40 | 3.8 | 30 | 5
Investigations
Decreased Hemoglobin | 34 | 19 | 29 | 16
Metabolism and nutrition disorders
Hypernatremia | 26 | 1.9 | 3.6 | 0
Hypokalemia | 15 | 9 | 1.8 | 0
Hypophosphatemia | 15 | 9 | 1.8 | 0
Hypermagnesemia | 11 | 9 | 5 | 3.6
General disorders
Pyrexia | 15 | 0 | 9 | 0

COG ACCL0431

The safety of PEDMARK was evaluated in COG ACCL0431 [see Clinical Studies (14)]. Patients received cisplatin-based chemotherapy with or without PEDMARK, administered at a dose that is bioequivalent to the recommended dose as an intravenous infusion over 15 minutes starting 6 hours after completion of each cisplatin infusion. Patients who received PEDMARK were treated for a median of 3 cycles (range: 1 to 6) during a median of 15 weeks of cisplatin-based chemotherapy.

Serious adverse reactions occurred in 36% of patients who received PEDMARK in combination with cisplatin-based chemotherapy. Serious adverse reactions in >5% of patients who received PEDMARK included febrile neutropenia, decreased neutrophil count, decreased platelet count, decreased white blood cell count, anemia, stomatitis, infections, decreased lymphocyte count, and increased alanine aminotransferase (ALT).

PEDMARK was permanently discontinued due to an adverse reaction in 1 patient; this patient discontinued PEDMARK for Grade 2 hypersensitivity.

The most common adverse reaction (≥25% with difference between arms of >5% compared to cisplatin alone) was hypokalemia.

Table 4 summarizes the adverse reactions reported in COG ACCL0431.

Table 4. Adverse Reactions (≥10%) in Patients Who Received PEDMARK and Cisplatin with a Difference Between Arms of >5% Compared to Cisplatin Alone in COG ACCL0431
Adverse Reaction | PEDMARK + Cisplatin (N = 59) |  | Cisplatin Alone (N = 64)
Adverse Reaction | All Grades (%) | Grade 3 or 4 (%) | All Grades (%) | Grade 3 or 4 (%)
Metabolism and nutrition disorders
Hypokalemia | 27 | 27 | 20 | 20
Hypophosphatemia | 20 | 20 | 11 | 11
Hyponatremia | 14 | 12 | 6 | 6
Hypernatremia | 12 | 0 | 6 | 0
Gastrointestinal disorders
Stomatitis | 14 | 14 | 6 | 6

6.2 Postmarketing Experience/Spontaneous Reports

The following adverse reactions have been identified from spontaneous reports based on medical literature. Because these reactions are reported voluntarily from a population of uncertain size, it is not always possible to reliably estimate their frequency or establish a causal relationship to drug exposure.

Cardiovascular Disorders: hypertension, hypotension

Metabolic and Nutritional Disorders: metabolic acidosis, hypocalcemia

8 USE IN SPECIFIC POPULATIONS

8.1 Pregnancy

Risk Summary

There are no available data on PEDMARK used in pregnant women to evaluate for a drug-associated risk. Oral or intravenous administration of sodium thiosulfate during the period of organogenesis resulted in no signs of malformations or lethality, but at doses and exposures that were lower than those in humans (see Data).

PEDMARK is administered following cisplatin infusions, which can cause embryo-fetal harm. Refer to cisplatin prescribing information for additional information.

In the U.S. general population, the estimated background risk of major birth defects and miscarriage in clinically recognized pregnancies is 2% to 4% and 15% to 20%, respectively.

Data

Animal Data

In animal studies, sodium thiosulfate was not embryotoxic or teratogenic in pregnant mice, rats, hamsters, or rabbits at daily (5 to 13 daily doses during the period of organogenesis) oral maternal doses of up to 550, 400, 400, and 580 mg/kg/day (0.08 to 0.35 times the highest clinical dose of 20 g/m^2 based on body surface area [BSA]), respectively, of sodium thiosulfate; exposure in these animals compared to humans may be much lower due to poor oral bioavailability. Sodium thiosulfate was not embryotoxic or teratogenic in hamsters following a total daily dose of 1500 mg/kg (0.38 times the highest clinical dose of 20 g/m^2 based on BSA). Additionally, an intravenous pharmacokinetic study in gravid ewes indicated that sodium thiosulfate does not cross the placenta.

8.2 Lactation

There are no data on the presence of sodium thiosulfate in human milk or its effects on the breastfed child or on milk production.

PEDMARK is administered in combination with cisplatin. Refer to cisplatin prescribing information for additional information.

8.4 Pediatric Use

The safety and effectiveness of PEDMARK have been established to reduce the risk of ototoxicity associated with cisplatin in pediatric patients 1 month of age and older with localized, non-metastatic solid tumors.

The safety and effectiveness of PEDMARK have not been established in pediatric patients younger than 1 month old or in pediatric patients with metastatic cancer.

PEDMARK is not recommended in pediatric patients younger than 1 month old due to the increased risk of hypernatremia [see Warnings and Precautions (5.2)].

8.6 Renal Impairment

Sodium thiosulfate is substantially excreted by the kidney [see Clinical Pharmacology (12.3)]. No dose adjustment is recommended for patients with renal impairment or end-stage renal disease. Monitor for signs and symptoms of hypernatremia and hypokalemia more closely if the GFR falls below 60 mL/min/1.73 m^2 [see Warnings and Precautions (5.2)].

11 DESCRIPTION

Sodium thiosulfate anhydrous is an inorganic salt with a molecular formula of Na2S2O3 and a molecular weight of 158.11 g/mol. The structural formula is:

It is a white to off-white crystalline solid that is soluble in water, but insoluble in alcohol. The aqueous solution has a pH ranging from 6.5 to 8.0.

PEDMARK (sodium thiosulfate injection) is a sterile, preservative-free, clear, colorless solution in a single-dose vial for intravenous use with a pH between 7 and 9. Each vial contains the equivalent of 12.5 grams of sodium thiosulfate pentahydrate (provided as sodium thiosulfate anhydrous 8 grams) in 100 mL solution (125 mg/mL). Each mL contains the equivalent of 125 mg of sodium thiosulfate pentahydrate (provided as sodium thiosulfate anhydrous 80 mg) and 0.25 mg boric acid. Sodium hydroxide and hydrochloric acid may have been used for pH adjustment.

12 CLINICAL PHARMACOLOGY

12.1 Mechanism of Action

Cisplatin-induced ototoxicity is caused by irreversible damage to hair cells in the cochlea hypothesized to be due to a combination of reactive oxygen species (ROS) production and direct alkylation of DNA leading to cell death. Sodium thiosulfate interacts directly with cisplatin to produce an inactive platinum species. In addition, sodium thiosulfate can enter cells through the sodium sulfate cotransporter 2 and cause intracellular effects such as the increase in antioxidant glutathione levels and inhibition of intracellular oxidative stress. Both activities may contribute to the ability of sodium thiosulfate to reduce the risk of ototoxicity.

Concurrent incubation of sodium thiosulfate with cisplatin decreased the in vitro cytotoxicity of cisplatin to tumor cells; delaying the addition of sodium thiosulfate to these cultures prevented the protective effect.

12.2 Pharmacodynamics

Serum Sodium Level

A 20 g/m^2 dose delivers a sodium load of 162 mmol/m^2, a 15 g/m^2 dose delivers a sodium load of 121 mmol/m^2, and a 10 g/m^2 dose delivers a sodium load of 81 mmol/m^2. In SIOPEL 6, the recommended dosage resulted in an average transient increase in serum sodium levels of approximately 6 mmol/L at 1 hour after infusion [see Warnings and Precautions (5.2)] and levels had returned to baseline by 18 hours or 24 hours after administration.

12.3 Pharmacokinetics

The pharmacokinetics (PK) of thiosulfate was assessed in pediatric patients. At the recommended dosage, the mean (±SD) maximum concentration (Cmax) was 13 ± 1.2 mM. The Cmax of thiosulfate increased proportionally to dose over the range of 4 g/m^2 to 20 g/m^2. No accumulation of thiosulfate is expected following administration of PEDMARK on two consecutive days.

Distribution

Sodium thiosulfate does not bind to human plasma proteins. Sodium thiosulfate is an inorganic salt and thiosulfate anions do not readily cross cell membranes. The mean volume of distribution of thiosulfate is 0.23 L/kg.

Elimination

The mean half-life (t1/2) of thiosulfate is approximately 20 minutes to 50 minutes. The mean total clearance of thiosulfate is 2.2 mL/min/kg in patients with fully developed renal function (age approximately 1 year). Renal clearance accounts for approximately 50% of total clearance in patients with fully developed renal function.

Metabolism

Thiosulfate is an endogenous intermediate product of sulfur-containing amino acid metabolism. Thiosulfate is metabolized through thiosulfate sulfur transferase and thiosulfate reductase to sulfite, which is oxidized to sulfate.

Excretion

After administration of sodium thiosulfate, approximately 50% of the administered sodium thiosulfate was excreted unchanged in urine and >95% of the dose excreted in urine occurs within the first 4 hours after administration.

Specific Populations

Patients with Renal Impairment

Thiosulfate Cmax increased approximately 25% and AUC increased approximately 2-fold in subjects on hemodialysis (GFR 0 to 6 mL/min/1.72 m^2, estimated by the modification of diet in renal disease [MDRD] equation) compared to subjects with normal renal function (GFR >70 mL/min/1.72 m^2, MDRD).

Drug Interaction Studies

In Vitro Studies

Cytochrome P450 Enzymes: Sodium thiosulfate is an inducer of CYP2B6 but not of CYP1A2 or CYP3A4. Sodium thiosulfate is not an inhibitor of CYP1A2, CYP2B6, CYP2C8, CYP2C9, CYP2C19, CYP2D6 or CYP3A4 at clinically relevant concentrations.

13 NONCLINICAL TOXICOLOGY

13.1 Carcinogenesis, Mutagenesis, Impairment of Fertility

Long-term studies in animals have not been performed to evaluate the potential carcinogenicity of sodium thiosulfate. In an in vitro Bacterial Reverse Mutation Assay (Ames Assay), sodium thiosulfate was not mutagenic in the absence of metabolic activation in S. typhimurium strains TA98, TA100, TA1535, TA1537, or TA1538, nor in the presence of metabolic activation in strains TA98, TA1535, TA1537, or TA1538 or E. coli strain WP2. Sodium thiosulfate at up to 1000 µM did not increase the frequency of sister chromatid exchanges in human lymphocytes in vitro.

There are no animal studies examining the effects of sodium thiosulfate on fertility.

14 CLINICAL STUDIES

The efficacy of PEDMARK in reducing the risk of cisplatin-associated ototoxicity was evaluated in two multicenter studies: SIOPEL 6 and COG ACCL0431.

SIOPEL 6

SIOPEL 6 (NCT00652132) was a multicenter, randomized, controlled, open-label study. Eligible patients were between 1 month and 18 years of age and were receiving cisplatin-based chemotherapy for standard-risk hepatoblastoma. Patients were randomized 1:1 to receive 6 cycles of perioperative cisplatin-based chemotherapy without (cisplatin alone arm) or with PEDMARK (PEDMARK + cisplatin arm). Patients received PEDMARK at a dose based on body weight administered intravenously over 15 minutes, beginning 6 hours after completion of each cisplatin infusion. Doses of PEDMARK were 10 g/m^2 for patients weighing <5 kg; 15 g/m^2 for patients weighing 5 kg to 10 kg; and 20 g/m^2 for patients weighing >10 kg. Randomization was stratified by country, age (above vs below 15 months), and PRETEXT (I and II vs III). The major efficacy outcome measure was hearing loss defined as a Brock Grade ≥1; hearing was assessed using pure tone audiometry after study treatment or at an age of at least 3.5 years, whichever was later.

A total of 114 patients were randomized, 61 patients to the PEDMARK + cisplatin arm and 53 patients to the cisplatin alone arm. The median age was 1.1 years (range: 1.2 months to 8.2 years); 55% were male; 60% were White, 11% were Asian, and 1.8% were Black or African American.

The incidence of hearing loss was lower in the PEDMARK + cisplatin arm compared with the cisplatin alone arm. Efficacy results are provided in Table 5.

Table 5: Efficacy Results for SIOPEL 6
Patients Who Experienced Hearing Loss | PEDMARK + Cisplatin (N = 61 [6 patients who received PEDMARK + cisplatin and 7 patients who received cisplatin alone did not have hearing assessed and were assumed to have hearing loss.]) | Cisplatin Alone (N = 53)
Yes, n (%) | 24 (39) | 36 (68)
No, n (%) | 37 (61) | 17 (32)
Unadjusted relative risk (95% CI) | 0.58 (0.40, 0.83)
Adjusted relative risk (95% CI) [From Cochran-Mantel-Haenszel test stratified by country group, age group, and PRETEXT group] | 0.58 (0.41, 0.81)

COG ACCL0431

COG ACCL0431 (NCT00716976) was a multicenter, randomized, controlled, open-label study. Eligible patients were between 1 and 18 years of age and were receiving a chemotherapy regimen that included a cumulative cisplatin dose of 200 mg/m^2 or higher, with individual cisplatin doses to be infused over 6 hours or less. Patients were randomized 1:1 to receive cisplatin-based chemotherapy without (cisplatin alone arm) or with PEDMARK (PEDMARK + cisplatin arm). Cisplatin was administered according to each site's disease-specific treatment protocols. Patients received PEDMARK intravenously starting 6 hours after the completion of each cisplatin infusion, at a dose bioequivalent to the recommended dose. The PEDMARK infusion must have been completed at least 10 hours before the next cisplatin infusion if the treatment protocol required multiple daily doses of cisplatin. Randomization was stratified by prior cranial radiation (yes vs no); for patients without prior cranial radiation, randomization was further stratified by age (<5 years vs ≥5 years) and duration of cisplatin infusion (<2 hours vs ≥2 hours). The major efficacy outcome measure was hearing loss assessed by American Speech-Language-Hearing Association (ASHA) criteria; hearing was assessed at baseline and 4 weeks after the final course of cisplatin.

A total of 125 pediatric patients were randomized, 61 patients to the PEDMARK + cisplatin arm and 64 patients to the cisplatin alone arm. The efficacy was evaluated in patients with localized disease in the ITT population (n = 77). The median age was 8 years (range: 1 to 18); 61% were male; 62% were White, 14% were Black or African American, and 2.6% were Asian. The median Karnofsky or Lansky performance status was 90 (range: 50 to 100). Underlying diagnosis included medulloblastoma (27%), osteosarcoma (26%), germ cell tumor (23%), neuroblastoma (10%), hepatoblastoma (8%), atypical teratoid/rhabdoid tumor (2.6%), choroid plexus carcinoma (1.3%), and anaplastic astrocytoma (1.3%); 7% had prior cranial radiation.

The incidence of hearing loss was lower in the PEDMARK + cisplatin arm compared with the cisplatin alone arm. Efficacy results are provided in Table 6.

Table 6: Efficacy Results for COG ACCL0431 – Patients with Localized Disease
Patients Who Experienced Hearing Loss | PEDMARK + Cisplatin (N = 39 [8 patients who received PEDMARK + cisplatin and 5 patients who received cisplatin alone did not have hearing assessed and were assumed to have hearing loss.]) | Cisplatin Alone (N = 38)
Yes, n (%) | 17 (44) | 22 (58)
No, n (%) | 22 (56) | 16 (42)
Unadjusted relative risk (95% CI) | 0.75 (0.48, 1.18)
Adjusted relative risk (95% CI) [From Cochran-Mantel-Haenszel test stratified by prior cranial irradiation, age group, and duration of cisplatin infusion] | 0.84 (0.53, 1.35)

16 HOW SUPPLIED/STORAGE AND HANDLING

PEDMARK (sodium thiosulfate injection) is a clear, colorless, sterile solution in a Type 1 Plus borosilicate glass single-dose vial with rubber stopper and capped with aluminum overseal, supplied as:

- 12.5 grams/100 mL (125 mg/mL) single-dose vial, NDC 73077-010-01

STORAGE AND HANDLING

Store at 20°C to 25°C (68°F to 77°F); excursions are permitted between 15°C and 30°C (59°F to 86°F).

17 PATIENT COUNSELING INFORMATION

Advise the patient to read the FDA-approved patient labeling (Patient Information).

Hypersensitivity

Inform patients and caregivers that PEDMARK can cause hypersensitivity reactions [see Warnings and Precautions (5.1)].

Hypernatremia and Hypokalemia

Inform patients and caregivers that PEDMARK can cause hypernatremia and hypokalemia, and to promptly report signs and symptoms consistent with these electrolyte abnormalities [see Warnings and Precautions (5.2)].

Nausea and Vomiting

Inform patients and caregivers that PEDMARK can cause nausea and vomiting [see Warnings and Precautions (5.3)].

Distributed by Fennec Pharmaceuticals, Inc., 221 River Street, Hoboken, NJ 07030

PEDMARK is a registered trademark of Fennec Pharmaceuticals Inc.

US PATENTS 10,792,363; 11,291,728, 11,964,018, 11,992,530, 11,998,604.

PRINCIPAL DISPLAY PANEL - 100 mL Vial Box

100 mL
Sterile

NDC 73077-010-01

pedmark®
(sodium thiosulfate injection)

12.5 grams/100 mL (125 mg/mL)

For Intravenous Use Only
Single-Dose Vial. Discard Unused
Portion.

Rx Only

Do Not Substitute with Other
Sodium Thiosulfate Products